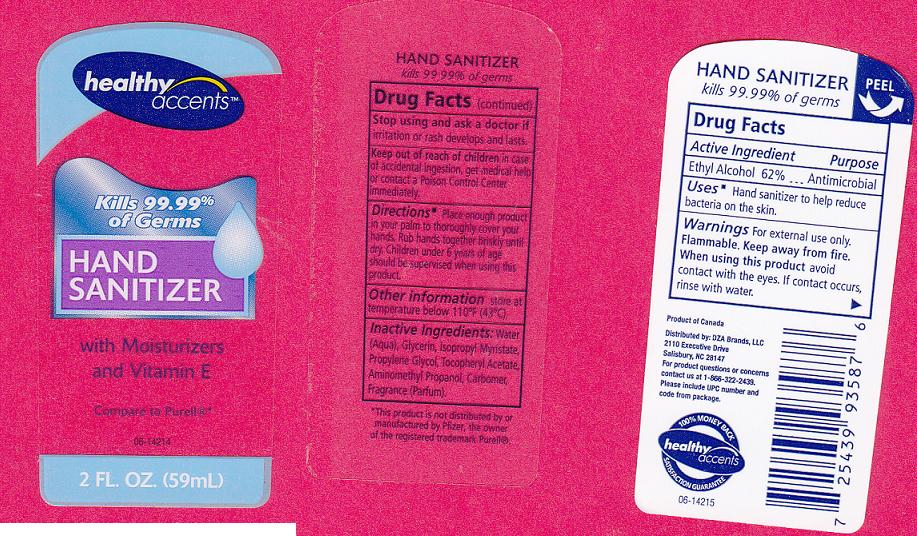 DRUG LABEL: HAND SANITIZER
NDC: 55316-268 | Form: GEL
Manufacturer: DZA BRANDS LLC
Category: otc | Type: HUMAN OTC DRUG LABEL
Date: 20110314

ACTIVE INGREDIENTS: ALCOHOL 62 mL/100 mL
INACTIVE INGREDIENTS: WATER; GLYCERIN; ISOPROPYL MYRISTATE; PROPYLENE GLYCOL; .ALPHA.-TOCOPHEROL ACETATE, D-; AMINOMETHYLPROPANOL; CARBOMER 934

DRUG FACTS

ACTIVE INGREDIENT

ETHYL ALCOHOL 62%

PURPOSE

ANTIMICROBIAL

USES

HAND SANITIZER TO HELP REDUCE BACTERIA ON THE SKIN.

WARNINGS

FOR EXTERNAL USE ONLY. FLAMMABLE. KEEP AWAY FROM FIRE.

WHEN USING THIS PRODUCT

AVOID CONTACT WITH THE EYES. IF CONTACT OCCURS, RINSE WITH WATER.

STOP USING AND ASK A DOCTOR IF

IRRITATION OR RASH DEVELOPS AND LASTS.

KEEP OUT OF REACH OF CHILDREN

IN CASE OF ACCIDENTAL INGESTION, GET MEDICAL HELP OR CONTACT A POISON CONTROL CENTER IMMEDIATELY.

DIRECTIONS

PUT ENOUGH PRODUCT IN YOUR PALM TO THROUGHLY COVER YOUR HANDS. RUB HANDS TOGETHER BRISKLY UNTIL DRY. CHILDREN UNDER 6 YEARS OF AGE SHOULD BE SUPERVISED WHEN USING THIS PRODUCT.

OTHER INFORMATION

STORE AT A TEMPERATURE BELOW 110 FAHRENHEIT (43 DEGREES CELCIUS).

INACTIVE INGREDIENT

WATER, GLYCERIN, ISOPROPYL MYRISTATE, PROPYLENE GLYCOL, TOCOPHERYL ACETATE, AMINOMETHYL PROPANOL, CARBOMER, FRAGRANCE.